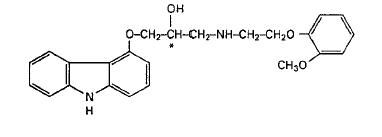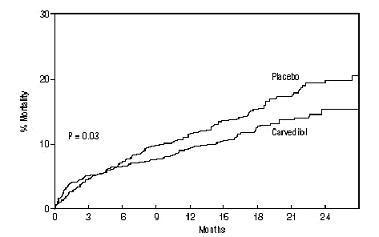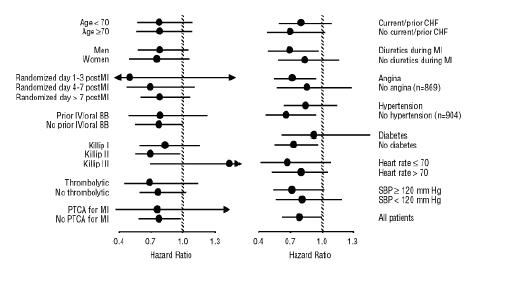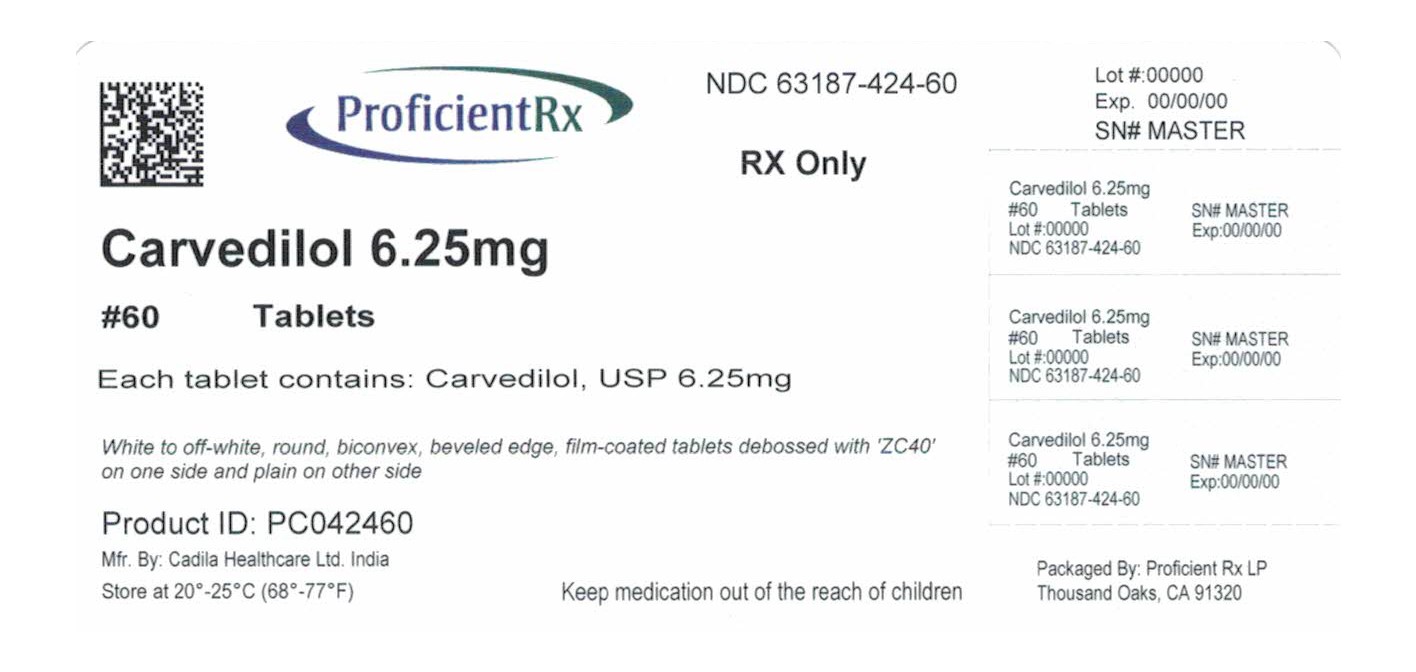 DRUG LABEL: Carvedilol
NDC: 63187-424 | Form: TABLET, FILM COATED
Manufacturer: Proficient Rx LP
Category: prescription | Type: HUMAN PRESCRIPTION DRUG LABEL
Date: 20251201

ACTIVE INGREDIENTS: CARVEDILOL 6.25 mg/1 1
INACTIVE INGREDIENTS: AMINOLEVULINIC ACID HYDROCHLORIDE; AMINOMETRADINE; AMINOPENTAMIDE SULFATE; AMINOPHYLLINE; AMINOPROMAZINE; AMINOPROMAZINE MONOFUMARATE; AMINOPTERIN SODIUM; VISNAGA DAUCOIDES FRUIT; AMOPROXAN; CROSPOVIDONE (120 .MU.M); HYPROMELLOSE, UNSPECIFIED; LACTOSE MONOHYDRATE; MAGNESIUM STEARATE; POLYETHYLENE GLYCOL, UNSPECIFIED; SILICON DIOXIDE; POVIDONE, UNSPECIFIED; TALC; TITANIUM DIOXIDE

HIGHLIGHTS OF PRESCRIBING INFORMATION

These highlights do not include all the information needed to use carvedilol tablets safely and effectively. See full prescribing information for carvedilol tablets.
Initial U.S. Approval: 1995

RECENT MAJOR CHANGES

Warnings and Precautions, Major Surgery (5.9) October 2010

Warnings and Precautions, Intraoperative Floppy Iris Syndrome January 2011

(5.14)

1. INDICATIONS AND USAGE

Carvedilol tablets, USP is an alpha/beta-adrenergic blocking agent indicated for the treatment of:

- Left ventricular dysfunction following myocardial infarction in clinically stable patients(1.1)
- Hypertension(1.2)

2. DOSAGE AND ADMINISTRATION

Take with food. Individualize dosage and monitor during up-titration. (2)

- Left ventricular dysfunction following myocardial infarction: Start at 6.25 mg twice daily and increase to 12.5 mg then 25 mg twice daily after intervals of 3 to 10 days. A lower starting dose or slower titration may be used.(2.1)
- Hypertension: Start at 6.25 mg twice daily and increase if needed for blood pressure control to 12.5 mg then 25 mg twice daily over intervals of 1 to 2 weeks.(2.2)

3. DOSAGE FORMS AND STRENGTHS

Tablets: 3.125, 6.25, 12.5, 25 mg (3)

4. CONTRAINDICATIONS

- Bronchial asthma or related bronchospastic conditions (4)
- Second- or third-degree AV block (4)
- Sick sinus syndrome (4)
- Severe bradycardia (unless permanent pacemaker in place) (4)
- Patients in cardiogenic shock or decompensated heart failure requiring the use of IV inotropic therapy. (4)
- Severe hepatic impairment (2.3, 4)
- History of serious hypersensitivity reaction (e.g., Stevens-Johnson syndrome, anaphylactic reaction, angioedema) to carvedilol, any of the components of carvedilol (4)

5. WARNINGS AND PRECAUTIONS

- Acute exacerbation of coronary artery disease upon cessation of therapy: Do not abruptly discontinue. (5.1)
- Bradycardia, hypotension, worsening heart failure/fluid retention may occur. Reduce the dose as needed. (5.2, 5.3, 5.4)
- Non-allergic bronchospasm (e.g., chronic bronchitis and emphysema): Avoid β-blockers. (4) However, if deemed necessary, use with caution and at lowest effective dose. (5.5)
- Diabetes: Monitor glucose as β-blockers may mask symptoms of hypoglycemia or worsen hyperglycemia. (5.6)

6. ADVERSE REACTIONS

Most common adverse events (6.1):

- Left ventricular dysfunction following myocardial infarction (≥10%): Dizziness, fatigue, hypotension, diarrhea, hyperglycemia, asthenia, bradycardia, weight increase
- Hypertension (≥5%): Dizziness

To report SUSPECTED ADVERSE REACTIONS, contact Zydus Pharmaceuticals USA Inc. at 1-877-993-8779 or FDA at 1-800-FDA-1088 or www.fda.gov/medwatch.

7. DRUG INTERACTIONS

- CYP P450 2D6 enzyme inhibitors may increase and rifampin may decrease carvedilol levels. (7.1, 7.5)
- Hypotensive agents (e.g., reserpine, MAO inhibitors, clonidine) may increase the risk of hypotension and/or severe bradycardia. (7.2)
- Cyclosporine or digoxin levels may increase. (7.3, 7.4)
- Both digitalis glycosides and β-blockers slow atrioventricular conduction and decrease heart rate. Concomitant use can increase the risk of bradycardia. (7.4)
- Amiodarone may increase carvedilol levels resulting in further slowing of the heart rate or cardiac conduction. (7.6)
- Verapamil- or diltiazem-type calcium channel blockers may affect ECG and/or blood pressure. (7.6)
- Insulin and oral hypoglycemics action may be enhanced. (7.7)

FULL PRESCRIBING INFORMATION

1. INDICATIONS AND USAGE

1.1 Left Ventricular Dysfunction Following Myocardial Infarction

Carvedilol tablets, USP are indicated to reduce cardiovascular mortality in clinically stable patients who have survived the acute phase of a myocardial infarction and have a left ventricular ejection fraction of ≤40% (with or without symptomatic heart failure) [see Clinical Studies (14.1)].

1.2 Hypertension

Carvedilol tablets, USP are indicated for the management of essential hypertension [see Clinical Studies (14.2)]. It can be used alone or in combination with other antihypertensive agents, especially thiazide-type diuretics [see Drug Interactions (7.2)].

2. DOSAGE AND ADMINISTRATION

Carvedilol should be taken with food to slow the rate of absorption and reduce the incidence of orthostatic effects.

2.1 Left Ventricular Dysfunction Following Myocardial Infarction

DOSAGE MUST BE INDIVIDUALIZED AND MONITORED DURING UP-TITRATION. Treatment with carvedilol tablets may be started as an inpatient or outpatient and should be started after the patient is hemodynamically stable and fluid retention has been minimized. It is recommended that carvedilol tablets be started at 6.25 mg twice daily and increased after 3 to 10 days, based on tolerability, to 12.5 mg twice daily, then again to the target dose of 25 mg twice daily. A lower starting dose may be used (3.125 mg twice daily) and/or the rate of up-titration may be slowed if clinically indicated (e.g., due to low blood pressure or heart rate, or fluid retention). Patients should be maintained on lower doses if higher doses are not tolerated. The recommended dosing regimen need not be altered in patients who received treatment with an IV or oral β-blocker during the acute phase of the myocardial infarction.

2.2 Hypertension

DOSAGE MUST BE INDIVIDUALIZED. The recommended starting dose of carvedilol tablets is 6.25 mg twice daily. If this dose is tolerated, using standing systolic pressure measured about 1 hour after dosing as a guide, the dose should be maintained for 7 to 14 days, and then increased to 12.5 mg twice daily if needed, based on trough blood pressure, again using standing systolic pressure one hour after dosing as a guide for tolerance. This dose should also be maintained for 7 to 14 days and can then be adjusted upward to 25 mg twice daily if tolerated and needed. The full antihypertensive effect of carvedilol tablet is seen within 7 to 14 days. Total daily dose should not exceed 50 mg.

Concomitant administration with a diuretic can be expected to produce additive effects and exaggerate the orthostatic component of carvedilol action.

2.3 Hepatic Impairment

Carvedilol tablets should not be given to patients with severe hepatic impairment [see CONTRAINDICATIONS (4)].

3. DOSAGE FORMS AND STRENGTHS

The white to off-white, round, film-coated tablets are available in the following strengths: 3.125 mg– debossed with Z and 1, 6.25 mg–debossed with ZC40, 12.5 mg–debossed with ZC41 and 25 mg–debossed with ZC42.

4. CONTRAINDICATIONS

Carvedilol tablets are contraindicated in the following conditions:

- Bronchial asthma or related bronchospastic conditions. Deaths from status asthmaticus have been reported following single doses of carvedilol tablets.
- Second- or third-degree AV block
- Sick sinus syndrome
- Severe bradycardia (unless a permanent pacemaker is in place)
- Patients with cardiogenic shock or who have decompensated heart failure requiring the use of intravenous inotropic therapy. Such patients should first be weaned from intravenous therapy before initiating carvedilol tablets
- Patients with severe hepatic impairment
- Patients with a history of a serious hypersensitivity reaction (e.g., Stevens-Johnson syndrome, anaphylactic reaction, angioedema) to carvedilol, any of the components of carvedilol tablets.

5. WARNINGS AND PRECAUTIONS

5.1 Cessation of Therapy

Patients with coronary artery disease, who are being treated with carvedilol tablets, should be advised against abrupt discontinuation of therapy. Severe exacerbation of angina and the occurrence of myocardial infarction and ventricular arrhythmias have been reported in angina patients following the abrupt discontinuation of therapy with β-blockers. The last 2 complications may occur with or without preceding exacerbation of the angina pectoris. As with other β-blockers, when discontinuation of carvedilol tablets is planned, the patients should be carefully observed and advised to limit physical activity to a minimum. Carvedilol tablets should be discontinued over 1 to 2 weeks whenever possible. If the angina worsens or acute coronary insufficiency develops, it is recommended that carvedilol tablets be promptly reinstituted, at least temporarily. Because coronary artery disease is common and may be unrecognized, it may be prudent not to discontinue therapy with carvedilol abruptly even in patients treated only for hypertension or heart failure.

5.2 Bradycardia

In clinical trials, carvedilol tablets caused bradycardia in about 2% of hypertensive patients, and 6.5% of myocardial infarction patients with left ventricular dysfunction. If pulse rate drops below 55 beats/minute, the dosage should be reduced.

5.3 Hypotension

Postural hypotension occurred in 1.8% and syncope in 0.1% of hypertensive patients, primarily following the initial dose or at the time of dose increase and was a cause for discontinuation of therapy in 1% of patients.

In the CAPRICORN study of survivors of an acute myocardial infarction, hypotension or postural hypotension occurred in 20.2% of patients receiving carvedilol tablets compared to 12.6% of placebo patients. Syncope was reported in 3.9% and 1.9% of patients, respectively. These events were a cause for discontinuation of therapy in 2.5% of patients receiving carvedilol tablets, compared to 0.2% of placebo patients.

Starting with a low dose, administration with food, and gradual up-titration should decrease the likelihood of syncope or excessive hypotension [see DOSAGE AND ADMINISTRATION (2.1, 2.2)]. During initiation of therapy, the patient should be cautioned to avoid situations such as driving or hazardous tasks, where injury could result should syncope occur.

5.4 Heart Failure/Fluid Retention

Worsening heart failure or fluid retention may occur during up-titration of carvedilol. If such symptoms occur, diuretics should be increased and the carvedilol dose should not be advanced until clinical stability resumes [see DOSAGE AND ADMINISTRATION (2)]. Occasionally it is necessary to lower the carvedilol dose or temporarily discontinue it. Such episodes do not preclude subsequent successful titration of, or a favorable response to, carvedilol.

5.5 Non-allergic Bronchospasm

Patients with bronchospastic disease (e.g., chronic bronchitis and emphysema) should, in general, not receive β-blockers. Carvedilol tablets may be used with caution, however, in patients who do not respond to, or cannot tolerate, other antihypertensive agents. It is prudent, if carvedilol tablets are used, to use the smallest effective dose, so that inhibition of endogenous or exogenous β-agonists is minimized.

In clinical trials, patients with bronchospastic disease were enrolled if they did not require oral or inhaled medication to treat their bronchospastic disease. In such patients, it is recommended that carvedilol be used with caution. The dosing recommendations should be followed closely and the dose should be lowered if any evidence of bronchospasm is observed during up-titration.

5.6 Glycemic Control in Type 2 Diabetes

In general, β-blockers may mask some of the manifestations of hypoglycemia, particularly tachycardia. Nonselective β-blockers may potentiate insulin-induced hypoglycemia and delay recovery of serum glucose levels. Patients subject to spontaneous hypoglycemia, or diabetic patients receiving insulin or oral hypoglycemic agents, should be cautioned about these possibilities.

Studies designed to examine the effects of carvedilol on glycemic control in patients with diabetes and heart failure have not been conducted.

In a study designed to examine the effects of carvedilol on glycemic control in a population with mild-to-moderate hypertension and well-controlled type 2 diabetes mellitus, carvedilol had no adverse effect on glycemic control, based on HbA1c measurements [see CLINICAL STUDIES (14.4)].

5.7 Peripheral Vascular Disease

β-blockers can precipitate or aggravate symptoms of arterial insufficiency in patients with peripheral vascular disease. Caution should be exercised in such individuals.

5.8 Deterioration of Renal Function

Rarely, use of carvedilol in patients with heart failure has resulted in deterioration of renal function. Patients at risk appear to be those with low blood pressure (systolic blood pressure <100 mm Hg), ischemic heart disease and diffuse vascular disease, and/or underlying renal insufficiency. Renal function has returned to baseline when carvedilol was stopped. In patients with these risk factors it is recommended that renal function be monitored during up-titration of carvedilol and the drug discontinued or dosage reduced if worsening of renal function occurs.

5.9 Major Surgery

Chronically administered beta-blocking therapy should not be routinely withdrawn prior to major surgery; however, the impaired ability of the heart to respond to reflex adrenergic stimuli may augment the risks of general anesthesia and surgical procedures.

5.10 Thyrotoxicosis

β-adrenergic blockade may mask clinical signs of hyperthyroidism, such as tachycardia. Abrupt withdrawal of β-blockade may be followed by an exacerbation of the symptoms of hyperthyroidism or may precipitate thyroid storm.

5.11 Pheochromocytoma

In patients with pheochromocytoma, an α-blocking agent should be initiated prior to the use of any β-blocking agent. Although carvedilol has both α- and β-blocking pharmacologic activities, there has been no experience with its use in this condition. Therefore, caution should be taken in the administration of carvedilol to patients suspected of having pheochromocytoma.

5.12 Prinzmetal’s Variant Angina

Agents with non-selective β-blocking activity may provoke chest pain in patients with Prinzmetal's variant angina. There has been no clinical experience with carvedilol in these patients although the α-blocking activity may prevent such symptoms. However, caution should be taken in the administration of carvedilol to patients suspected of having Prinzmetal's variant angina.

5.13 Risk of Anaphylactic Reaction

While taking β-blockers, patients with a history of severe anaphylactic reaction to a variety of allergens may be more reactive to repeated challenge, either accidental, diagnostic, or therapeutic. Such patients may be unresponsive to the usual doses of epinephrine used to treat allergic reaction.

5.14 Intraoperative Floppy Iris Syndrome

Intraoperative Floppy Iris Syndrome (IFIS) has been observed during cataract surgery in some patients treated with alpha-1 blockers (carvedilol is an alpha/beta blocker). This variant of small pupil syndrome is characterized by the combination of a flaccid iris that billows in response to intraoperative irrigation currents, progressive intraoperative miosis despite preoperative dilation with standard mydriatic drugs, and potential prolapse of the iris toward the phacoemulsification incisions. The patient's ophthalmologist should be prepared for possible modifications to the surgical technique, such as utilization of iris hooks, iris dilator rings, or viscoelastic substances. There does not appear to be a benefit of stopping alpha-1 blocker therapy prior to cataract surgery.

6. ADVERSE REACTIONS

6.1 Clinical Studies Experience

Carvedilol tablets have been evaluated for safety in patients with left ventricular dysfunction following myocardial infarction and in hypertensive patients. The observed adverse event profile was consistent with the pharmacology of the drug and the health status of the patients in the clinical trials. Adverse events reported for each of these patient populations are provided below. Excluded are adverse events considered too general to be informative, and those not reasonably associated with the use of the drug because they were associated with the condition being treated or are very common in the treated population. Rates of adverse events were generally similar across demographic subsets (men and women, elderly and non-elderly, blacks and non-blacks).

Left Ventricular Dysfunction Following Myocardial Infarction:

Carvedilol tablets have been evaluated for safety in survivors of an acute myocardial infarction with left ventricular dysfunction in the CAPRICORN trial which involved 969 patients who received carvedilol tablets and 980 who received placebo. Approximately 75% of the patients received carvedilol tablets for at least 6 months and 53% received carvedilol tablets for at least 12 months. Patients were treated for an average of 12.9 months and 12.8 months with carvedilol tablets and placebo, respectively.

The following adverse events were reported with a frequency of >1% but ≤3% and more frequently with carvedilol tablets: flu syndrome, cerebrovascular accident, peripheral vascular disorder, hypotonia, depression, gastrointestinal pain, arthritis, and gout. The overall rates of discontinuations due to adverse events were similar in both groups of patients. In this database, the only cause of discontinuation >1%, and occurring more often on carvedilol was hypotension (1.5% on carvedilol, 0.2% on placebo).

Hypertension:

Carvedilol tablets have been evaluated for safety in hypertension in more than 2,193 patients in US clinical trials and in 2,976 patients in international clinical trials. Approximately 36% of the total treated population received carvedilol tablets for at least 6 months. Most adverse events reported during therapy with carvedilol tablets were of mild to moderate severity. In US controlled clinical trials directly comparing carvedilol tablets in doses up to 50 mg (n = 1,142) to placebo (n = 462), 4.9% of patients receiving carvedilol tablets discontinued for adverse events versus 5.2% of placebo patients. Although there was no overall difference in discontinuation rates, discontinuations were more common in the carvedilol group for postural hypotension (1% versus 0). The overall incidence of adverse events in US placebo-controlled trials increased with increasing dose of carvedilol tablets. For individual adverse events this could only be distinguished for dizziness, which increased in frequency from 2% to 5% as total daily dose increased from 6.25 mg to 50 mg.

Table 1 shows adverse events in US placebo-controlled clinical trials for hypertension that occurred with an incidence of >1% regardless of causality, and that were more frequent in drug-treated patients than placebo-treated patients.

Table 1 Adverse Events (%) Occurring in US Placebo-Controlled Hypertension Trials (Incidence ≥1%, Regardless of Causality) [Shown are events with rate >1% rounded to nearest integer.]
 | Carvedilol Tablets | Placebo
 | (n = 1,142) | (n = 462)
Cardiovascular
Bradycardia | 2 | -
Postural hypotension | 2 | -
Peripheral edema | 1 | -
Central Nervous System
Dizziness | 6 | 5
Insomnia | 2 | 1
Gastrointestinal
Diarrhea | 2 | 1
Hematologic
Thrombocytopenia | 1 | -
Metabolic
Hypertriglyceridemia | 1 | -

Dyspnea and fatigue were also reported in these studies, but the rates were equal or greater in patients who received placebo.

The following adverse events not described above were reported as possibly or probably related to carvedilol tablets in worldwide open or controlled trials with carvedilol tablets in patients with hypertension.

Incidence >0.1% to ≤1%

Cardiovascular:

Peripheral ischemia, tachycardia.

Central and Peripheral Nervous System:

Hypokinesia.

Gastrointestinal:

Bilirubinemia, increased hepatic enzymes (0.2% of hypertension patients were discontinued from therapy because of increases in hepatic enzymes) [see Adverse Reactions (6.2)].

Psychiatric:

Nervousness, sleep disorder, aggravated depression, impaired concentration, abnormal thinking, paroniria, emotional lability.

Respiratory System:

Asthma [see CONTRAINDICATIONS (4)].

Reproductive, male:

Decreased libido.

Skin and Appendages:

Pruritus, rash erythematous, rash maculopapular, rash psoriaform, photosensitivity reaction.

Special Senses:

Tinnitus.

Urinary System:

Micturition frequency increased.

Autonomic Nervous System:

Dry mouth, sweating increased.

Metabolic and Nutritional:

Hypokalemia, hypertriglyceridemia.

Hematologic:

Anemia, leukopenia.

The following events were reported in ≤0.1% of patients and are potentially important: Complete AV block, bundle branch block, myocardial ischemia, cerebrovascular disorder, convulsions, migraine, neuralgia, paresis, anaphylactoid reaction, alopecia, exfoliative dermatitis, amnesia, GI hemorrhage, bronchospasm, pulmonary edema, decreased hearing, respiratory alkalosis, increased BUN, decreased HDL, pancytopenia, and atypical lymphocytes.

6.2 Laboratory Abnormalities

Reversible elevations in serum transaminases (ALT or AST) have been observed during treatment with carvedilol tablets. Rates of transaminase elevations (2- to 3-times the upper limit of normal) observed during controlled clinical trials have generally been similar between patients treated with carvedilol tablets and those treated with placebo. However, transaminase elevations, confirmed by rechallenge, have been observed with carvedilol tablets. In a long-term, placebo-controlled trial in severe heart failure, patients treated with carvedilol tablets had lower values for hepatic transaminases than patients treated with placebo, possibly because improvements in cardiac function induced by carvedilol led to less hepatic congestion and/or improved hepatic blood flow.

Carvedilol tablets have not been associated with clinically significant changes in serum potassium, total triglycerides, total cholesterol, HDL cholesterol, uric acid, blood urea nitrogen, or creatinine. No clinically relevant changes were noted in fasting serum glucose in hypertensive patients.

6.3 Postmarketing Experience

The following adverse reactions have been identified during post-approval use of carvedilol tablets. Because these reactions are reported voluntarily from a population of uncertain size, it is not always possible to reliably estimate their frequency or establish a causal relationship to drug exposure.

Blood and Lymphatic System Disorders

Aplastic anemia.

Immune System Disorders

Hypersensitivity (e.g., anaphylactic reactions, angioedema, urticaria).

Renal and Urinary Disorders

Urinary incontinence.

Respiratory, Thoracic and Mediastinal Disorders

Interstitial pneumonitis.

Skin and Subcutaneous Tissue Disorders

Stevens-Johnson syndrome, toxic epidermal necrolysis, erythema multiforme.

7. DRUG INTERACTIONS

7.1 CYP2D6 Inhibitors and Poor Metabolizers

Interactions of carvedilol with potent inhibitors of CYP2D6 isoenzyme (such as quinidine, fluoxetine, paroxetine, and propafenone) have not been studied, but these drugs would be expected to increase blood levels of the R(+) enantiomer of carvedilol [see CLINICAL PHARMACOLOGY (12.3)]. Retrospective analysis of side effects in clinical trials showed that poor 2D6 metabolizers had a higher rate of dizziness during up-titration, presumably resulting from vasodilating effects of the higher concentrations of the α-blocking R(+) enantiomer.

7.2 Hypotensive Agents

Patients taking both agents with β-blocking properties and a drug that can deplete catecholamines (e.g., reserpine and monoamine oxidase inhibitors) should be observed closely for signs of hypotension and/or severe bradycardia. Concomitant administration of clonidine with agents with β-blocking properties may potentiate blood-pressure and heart-rate-lowering effects. When concomitant treatment with agents with β-blocking properties and clonidine is to be terminated, the β-blocking agent should be discontinued first. Clonidine therapy can then be discontinued several days later by gradually decreasing the dosage.

7.3 Cyclosporine

Modest increases in mean trough cyclosporine concentrations were observed following initiation of carvedilol treatment in 21 renal transplant patients suffering from chronic vascular rejection. In about 30% of patients, the dose of cyclosporine had to be reduced in order to maintain cyclosporine concentrations within the therapeutic range, while in the remainder no adjustment was needed. On the average for the group, the dose of cyclosporine was reduced about 20% in these patients. Due to wide interindividual variability in the dose adjustment required, it is recommended that cyclosporine concentrations be monitored closely after initiation of carvedilol therapy and that the dose of cyclosporine be adjusted as appropriate.

7.4 Digitalis Glycosides

Both digitalis glycosides and β-blockers slow atrioventricular conduction and decrease heart rate. Concomitant use can increase the risk of bradycardia. Digoxin concentrations are increased by about 15% when digoxin and carvedilol are administered concomitantly. Therefore, increased monitoring of digoxin is recommended when initiating, adjusting, or discontinuing Carvedilol tablets [see CLINICAL PHARMACOLOGY (12.5)].

7.5 Inducers/Inhibitors of Hepatic Metabolism

Rifampin reduced plasma concentrations of carvedilol by about 70% [see CLINICAL PHARMACOLOGY (12.5)]. Cimetidine increased AUC by about 30% but caused no change in Cmax [see CLINICAL PHARMACOLOGY (12.5)].

7.6 Amiodarone

Amiodarone, and its metabolite desethyl amiodarone, inhibitors of CYP2C9 and P385 glycoprotein, increased concentrations of the S(-) enantiomer of carvedilol by at least 2-fold [see CLINICAL PHARMACOLOGY(12.5)]. The concomitant administration of amiodarone or other CYP2C9 inhibitors such as fluconazole with carvedilol may enhance the β-blocking properties of carvedilol resulting in further slowing of the heart rate or cardiac conduction. Patients should be observed for signs of bradycardia or heart block, particularly when one agent is added to pre-existing treatment with the other.

7.7 Calcium Channel Blockers

Conduction disturbance (rarely with hemodynamic compromise) has been observed when carvedilol tablet is co-administered with diltiazem. As with other agents with β-blocking properties, if carvedilol tablet is to be administered with calcium channel blockers of the verapamil or diltiazem type, it is recommended that ECG and blood pressure be monitored.

7.8 Insulin or Oral Hypoglycemics

Agents with β-blocking properties may enhance the blood-sugar-reducing effect of insulin and oral hypoglycemics. Therefore, in patients taking insulin or oral hypoglycemics, regular monitoring of blood glucose is recommended [see WARNINGS AND PRECAUTIONS (5.6)].

7.9 Anesthesia

If treatment with carvedilol extended-release capsules is to be continued perioperatively, particular care should be taken when anesthetic agents which depress myocardial function, such as ether, cyclopropane, and trichloroethylene, are used [see OVERDOSAGE (10)].

8. USE IN SPECIFIC POPULATIONS

8.1 Pregnancy

Pregnancy Category C. Studies performed in pregnant rats and rabbits given carvedilol revealed increased post-implantation loss in rats at doses of 300 mg/kg/day (50 times the maximum recommended human dose [MRHD] as mg/m^2) and in rabbits at doses of 75 mg/kg/day (25 times the MRHD as mg/m^2). In the rats, there was also a decrease in fetal body weight at the maternally toxic dose of 300 mg/kg/day (50 times the MRHD as mg/m^2), which was accompanied by an elevation in the frequency of fetuses with delayed skeletal development (missing or stunted 13th rib). In rats the no-observed-effect level for developmental toxicity was 60 mg/kg/day (10 times the MRHD as mg/m^2); in rabbits it was 15 mg/kg/day (5 times the MRHD as mg/m^2). There are no adequate and well-controlled studies in pregnant women. Carvedilol tablets should be used during pregnancy only if the potential benefit justifies the potential risk to the fetus.

8.3 Nursing Mothers

It is not known whether this drug is excreted in human milk. Studies in rats have shown that carvedilol and/or its metabolites (as well as other β-blockers) cross the placental barrier and are excreted in breast milk. There was increased mortality at one week post-partum in neonates from rats treated with 60 mg/kg/day (10 times the MRHD as mg/m^2) and above during the last trimester through day 22 of lactation. Because many drugs are excreted in human milk and because of the potential for serious adverse reactions in nursing infants from β-blockers, especially bradycardia, a decision should be made whether to discontinue nursing or to discontinue the drug, taking into account the importance of the drug to the mother. The effects of other α- and β-blocking agents have included perinatal and neonatal distress.

8.4 Pediatric Use

Effectiveness of carvedilol tablets in patients younger than 18 years of age has not been established.

In a double-blind trial, 161 children (mean age 6 years, range 2 months to 17 years; 45% less than 2 years old) with chronic heart failure [NYHA class II-IV, left ventricular ejection fraction <40% for children with a systemic left ventricle (LV), and moderate-severe ventricular dysfunction qualitatively by echo for those with a systemic ventricle that was not an LV] who were receiving standard background treatment were randomized to placebo or to 2 dose levels of carvedilol. These dose levels produced placebo-corrected heart rate reduction of 4-6 heart beats per minute, indicative of β-blockade activity. Exposure appeared to be lower in pediatric subjects than adults. After 8 months of follow-up, there was no significant effect of treatment on clinical outcomes. Adverse reactions in this trial that occurred in greater than 10% of patients treated with carvedilol and at twice the rate of placebo-treated patients included chest pain (17% versus 6%), dizziness (13% versus 2%), and dyspnea (11% versus 0%).

8.5 Geriatric Use

Of the 975 myocardial infarction patients randomized to carvedilol tablets in the CAPRICORN trial, 48% (468) were 65 years of age or older, and 11% (111) were 75 years of age or older.

Of the 2,065 hypertensive patients in US clinical trials of efficacy or safety who were treated with carvedilol tablets, 21% (436) were 65 years of age or older. Of 3,722 patients receiving carvedilol tablets in hypertension clinical trials conducted worldwide, 24% were 65 years of age or older.

With the exception of dizziness in hypertensive patients (incidence 8.8% in the elderly versus 6% in younger patients), no overall differences in the safety or effectiveness (see Figure 2) were observed between the older subjects and younger subjects in each of these populations. Similarly, other reported clinical experience has not identified differences in responses between the elderly and younger subjects, but greater sensitivity of some older individuals cannot be ruled out.

10. OVERDOSAGE

Overdosage may cause severe hypotension, bradycardia, cardiac insufficiency, cardiogenic shock, and cardiac arrest. Respiratory problems, bronchospasms, vomiting, lapses of consciousness, and generalized seizures may also occur.

The patient should be placed in a supine position and, where necessary, kept under observation and treated under intensive-care conditions. Gastric lavage or pharmacologically induced emesis may be used shortly after ingestion. The following agents may be administered:

for excessive bradycardia: Atropine, 2 mg IV.

to support cardiovascular function: Glucagon, 5 to 10 mg IV rapidly over 30 seconds, followed by a continuous infusion of 5 mg/hour; sympathomimetics (dobutamine, isoprenaline, adrenaline) at doses according to body weight and effect.

If peripheral vasodilation dominates, it may be necessary to administer adrenaline or noradrenaline with continuous monitoring of circulatory conditions. For therapy-resistant bradycardia, pacemaker therapy should be performed. For bronchospasm, β-sympathomimetics (as aerosol or IV) or aminophylline IV should be given. In the event of seizures, slow IV injection of diazepam or clonazepam is recommended.

NOTE: In the event of severe intoxication where there are symptoms of shock, treatment with antidotes must be continued for a sufficiently long period of time consistent with the 7- to 10-hour half-life of carvedilol.

Cases of overdosage with carvedilol tablets alone or in combination with other drugs have been reported. Quantities ingested in some cases exceeded 1,000 milligrams. Symptoms experienced included low blood pressure and heart rate. Standard supportive treatment was provided and individuals recovered.

11. DESCRIPTION

Carvedilol is a nonselective β-adrenergic blocking agent with α1-blocking activity. It is (±)-1-(Carbazol-4-yloxy)-3-[[2-(o-methoxyphenoxy)ethyl]amino]-2-propanol. Carvedilol is a racemic mixture with the following structure:

Carvedilol, USP is a white to almost white crystalline powder with a molecular weight of 406.5 and a molecular formula of C24H26N2O4. It is freely soluble in dimethylsulfoxide; soluble in methylene chloride and methanol; sparingly soluble in 95% ethanol and isopropanol; slightly soluble in ethyl ether; and practically insoluble in water, gastric fluid (simulated, TS, pH 1.1), and intestinal fluid (simulated, TS without pancreatin, pH 7.5).

Each carvedilol tablet, USP intended for oral administration contains 3.125 mg or 6.25 mg or 12.5 mg or 25 mg of carvedilol. In addition, each tablet contains the following inactive ingredients: colloidal silicon dioxide, crospovidone, hypromellose, lactose monohydrate, magnesium stearate, polyethylene glycol, povidone, talc, and titanium dioxide.

The product meets USP Dissolution Test 3.

12. CLINICAL PHARMACOLOGY

12.1 Mechanism of Action

Carvedilol is a racemic mixture in which nonselective β-adrenoreceptor blocking activity is present in the S(-) enantiomer and α1-adrenergic blocking activity is present in both R(+) and S(-) enantiomers at equal potency. carvedilol has no intrinsic sympathomimetic activity.

12.2 Pharmacodynamics

Left Ventricular Dysfunction Following Myocardial Infarction:

The basis for the beneficial effects of carvedilol tablets in patients with left ventricular dysfunction following an acute myocardial infarction is not established.

Hypertension:

The mechanism by which β-blockade produces an antihypertensive effect has not been established.

β-adrenoreceptor blocking activity has been demonstrated in animal and human studies showing that carvedilol (1) reduces cardiac output in normal subjects; (2) reduces exercise- and/or isoproterenol-induced tachycardia; and (3) reduces reflex orthostatic tachycardia. Significant β-adrenoreceptor blocking effect is usually seen within 1 hour of drug administration.

α1-adrenoreceptor blocking activity has been demonstrated in human and animal studies, showing that carvedilol (1) attenuates the pressor effects of phenylephrine; (2) causes vasodilation; and (3) reduces peripheral vascular resistance. These effects contribute to the reduction of blood pressure and usually are seen within 30 minutes of drug administration.

Due to the α1-receptor blocking activity of carvedilol, blood pressure is lowered more in the standing than in the supine position, and symptoms of postural hypotension (1.8%), including rare instances of syncope, can occur. Following oral administration, when postural hypotension has occurred, it has been transient and is uncommon when carvedilol tablets is administered with food at the recommended starting dose and titration increments are closely followed [see DOSAGE AND ADMINISTRATION (2)].

In hypertensive patients with normal renal function, therapeutic doses of carvedilol tablets decreased renal vascular resistance with no change in glomerular filtration rate or renal plasma flow. Changes in excretion of sodium, potassium, uric acid, and phosphorus in hypertensive patients with normal renal function were similar after carvedilol tablets and placebo.

Carvedilol tablets have little effect on plasma catecholamines, plasma aldosterone, or electrolyte levels, but it does significantly reduce plasma renin activity when given for at least 4 weeks. It also increases levels of atrial natriuretic peptide.

12.3 Pharmacokinetics

Carvedilol is rapidly and extensively absorbed following oral administration, with absolute bioavailability of approximately 25% to 35% due to a significant degree of first-pass metabolism. Following oral administration, the apparent mean terminal elimination half-life of carvedilol generally ranges from 7 to 10 hours. Plasma concentrations achieved are proportional to the oral dose administered. When administered with food, the rate of absorption is slowed, as evidenced by a delay in the time to reach peak plasma levels, with no significant difference in extent of bioavailability. Taking carvedilol tablets with food should minimize the risk of orthostatic hypotension.

Carvedilol is extensively metabolized. Following oral administration of radiolabelled carvedilol to healthy volunteers, carvedilol accounted for only about 7% of the total radioactivity in plasma as measured by area under the curve (AUC). Less than 2% of the dose was excreted unchanged in the urine. Carvedilol is metabolized primarily by aromatic ring oxidation and glucuronidation. The oxidative metabolites are further metabolized by conjugation via glucuronidation and sulfation. The metabolites of carvedilol are excreted primarily via the bile into the feces. Demethylation and hydroxylation at the phenol ring produce 3 active metabolites with β-receptor blocking activity. Based on preclinical studies, the 4'-hydroxyphenyl metabolite is approximately 13 times more potent than carvedilol for β-blockade.

Compared to carvedilol, the 3 active metabolites exhibit weak vasodilating activity. Plasma concentrations of the active metabolites are about one-tenth of those observed for carvedilol and have pharmacokinetics similar to the parent.

Carvedilol undergoes stereoselective first-pass metabolism with plasma levels of R(+)-carvedilol approximately 2 to 3 times higher than S(-)-carvedilol following oral administration in healthy subjects. The mean apparent terminal elimination half-lives for R(+)-carvedilol range from 5 to 9 hours compared with 7 to 11 hours for the S(-)-enantiomer.

The primary P450 enzymes responsible for the metabolism of both R(+) and S(-)-carvedilol in human liver microsomes were CYP2D6 and CYP2C9 and to a lesser extent CYP3A4, 2C19, 1A2, and 2E1. CYP2D6 is thought to be the major enzyme in the 4'- and 5'-hydroxylation of carvedilol, with a potential contribution from 3A4. CYP2C9 is thought to be of primary importance in the O-methylation pathway of S(-)-carvedilol.

Carvedilol is subject to the effects of genetic polymorphism with poor metabolizers of debrisoquin (a marker for cytochrome P450 2D6) exhibiting 2- to 3-fold higher plasma concentrations of R(+)-carvedilol compared to extensive metabolizers. In contrast, plasma levels of S(-)-carvedilol are increased only about 20% to 25% in poor metabolizers, indicating this enantiomer is metabolized to a lesser extent by cytochrome P450 2D6 than R(+)-carvedilol. The pharmacokinetics of carvedilol do not appear to be different in poor metabolizers of S-mephenytoin (patients deficient in cytochrome P450 2C19).

Carvedilol is more than 98% bound to plasma proteins, primarily with albumin. The plasma-protein binding is independent of concentration over the therapeutic range. Carvedilol is a basic, lipophilic compound with a steady-state volume of distribution of approximately 115 L, indicating substantial distribution into extravascular tissues. Plasma clearance ranges from 500 to 700 mL/min.

12.4 Specific Populations

Geriatric:

Plasma levels of carvedilol average about 50% higher in the elderly compared to young subjects.

Hepatic Impairment:

Compared to healthy subjects, patients with severe liver impairment (cirrhosis) exhibit a 4- to 7-fold increase in carvedilol levels. Carvedilol is contraindicated in patients with severe liver impairment.

Renal Impairment:

Although carvedilol is metabolized primarily by the liver, plasma concentrations of carvedilol have been reported to be increased in patients with renal impairment. Based on mean AUC data, approximately 40% to 50% higher plasma concentrations of carvedilol were observed in hypertensive patients with moderate to severe renal impairment compared to a control group of hypertensive patients with normal renal function. However, the ranges of AUC values were similar for both groups. Changes in mean peak plasma levels were less pronounced, approximately 12% to 26% higher in patients with impaired renal function.

Consistent with its high degree of plasma protein-binding, carvedilol does not appear to be cleared significantly by hemodialysis.

12.5 Drug-Drug Interactions

Since carvedilol undergoes substantial oxidative metabolism, the metabolism and pharmacokinetics of carvedilol may be affected by induction or inhibition of cytochrome P450 enzymes.

Amiodarone:

In a pharmacokinetic study conducted in 106 Japanese patients with heart failure, coadministration of small loading and maintenance doses of amiodarone with carvedilol resulted in at least a 2-fold increase in the steady-state trough concentrations of S(-) carvedilol [see Drug Interactions(7.6) ].

Cimetidine:

In a pharmacokinetic study conducted in 10 healthy male subjects, cimetidine (1,000 mg/day) increased the steady-state AUC of carvedilol by 30% with no change in Cmax [see Drug Interactions (7.5)].

Digoxin:

Following concomitant administration of carvedilol (25 mg once daily) and digoxin (0.25 mg once daily) for 14 days, steady-state AUC and trough concentrations of digoxin were increased by 14% and 16%, respectively, in 12 hypertensive patients [see Drug Interactions(7.4)].

Glyburide:

In 12 healthy subjects, combined administration of carvedilol (25 mg once daily) and a single dose of glyburide did not result in a clinically relevant pharmacokinetic interaction for either compound.

Hydrochlorothiazide:

A single oral dose of carvedilol 25 mg did not alter the pharmacokinetics of a single oral dose of hydrochlorothiazide 25 mg in 12 patients with hypertension. Likewise, hydrochlorothiazide had no effect on the pharmacokinetics of carvedilol.

Rifampin:

In a pharmacokinetic study conducted in 8 healthy male subjects, rifampin (600 mg daily for 12 days) decreased the AUC and Cmax of carvedilol by about 70% [see Drug Interactions(7.5) ].

Torsemide:

In a study of 12 healthy subjects, combined oral administration of carvedilol 25 mg once daily and torsemide 5 mg once daily for 5 days did not result in any significant differences in their pharmacokinetics compared with administration of the drugs alone.

Warfarin:

Carvedilol (12.5 mg twice daily) did not have an effect on the steady-state prothrombin time ratios and did not alter the pharmacokinetics of R(+)- and S(-)-warfarin following concomitant administration with warfarin in 9 healthy volunteers.

13. NONCLINICAL TOXICOLOGY

13.1 Carcinogenesis, Mutagenesis, Impairment Of Fertility

In 2-year studies conducted in rats given carvedilol at doses up to 75 mg/kg/day (12 times the MRHD when compared on a mg/m^2 basis) or in mice given up to 200 mg/kg/day (16 times the MRHD on a mg/m^2 basis), carvedilol had no carcinogenic effect.

Carvedilol was negative when tested in a battery of genotoxicity assays, including the Ames and the CHO/HGPRT assays for mutagenicity and the in vitro hamster micronucleus and in vivo human lymphocyte cell tests for clastogenicity.

At doses ≥200 mg/kg/day (≥32 times the MRHD as mg/m^2) carvedilol was toxic to adult rats (sedation, reduced weight gain) and was associated with a reduced number of successful matings, prolonged mating time, significantly fewer corpora lutea and implants per dam, and complete resorption of 18% of the litters. The no-observed-effect dose level for overt toxicity and impairment of fertility was 60 mg/kg/day (10 times the MRHD as mg/m^2).

14. CLINICAL STUDIES

14.1 Left Ventricular Dysfunction Following Myocardial Infarction

CAPRICORN was a double-blind study comparing carvedilol and placebo in 1,959 patients with a recent myocardial infarction (within 21 days) and left ventricular ejection fraction of ≤40%, with (47%) or without symptoms of heart failure. Patients given carvedilol received 6.25 mg twice daily, titrated as tolerated to 25 mg twice daily. Patients had to have a systolic blood pressure >90 mm Hg, a sitting heart rate >60 beats/minute, and no contraindication to β-blocker use. Treatment of the index infarction included aspirin (85%), IV or oral β-blockers (37%), nitrates (73%), heparin (64%), thrombolytics (40%), and acute angioplasty (12%). Background treatment included ACE inhibitors or angiotensin receptor blockers (97%), anticoagulants (20%), lipid-lowering agents (23%), and diuretics (34%). Baseline population characteristics included an average age of 63 years, 74% male, 95% Caucasian, mean blood pressure 121/74 mm Hg, 22% with diabetes, and 54% with a history of hypertension. Mean dosage achieved of carvedilol was 20 mg twice daily; mean duration of follow-up was 15 months.

All-cause mortality was 15% in the placebo group and 12% in the carvedilol group, indicating a 23% risk reduction in patients treated with carvedilol (95% CI 2-40%, p = 0.03), as shown in Figure 1. The effects on mortality in various subgroups are shown in Figure 2. Nearly all deaths were cardiovascular (which were reduced by 25% by carvedilol), and most of these deaths were sudden or related to pump failure (both types of death were reduced by carvedilol). Another study end point, total mortality and all-cause hospitalization, did not show a significant improvement.

There was also a significant 40% reduction in fatal or non-fatal myocardial infarction observed in the group treated with carvedilol (95% CI 11% to 60%, p = 0.01). A similar reduction in the risk of myocardial infarction was also observed in a meta-analysis of placebo-controlled trials of carvedilol in heart failure.

Figure 1 Survival Analysis for CAPRICORN (intent-to-treat)

Figure 2. Effects on Mortality for Subgroups in CAPRICORN

14.2 Hypertension

Carvedilol tablets were studied in 2 placebo-controlled trials that utilized twice-daily dosing, at total daily doses of 12.5 to 50 mg. In these and other studies, the starting dose did not exceed 12.5 mg. At 50 mg/day, carvedilol tablets reduced sitting trough (12-hour) blood pressure by about 9/5.5 mm Hg; at 25 mg/day the effect was about 7.5/3.5 mm Hg. Comparisons of trough to peak blood pressure showed a trough to peak ratio for blood pressure response of about 65%. Heart rate fell by about 7.5 beats/minute at 50 mg/day. In general, as is true for other β-blockers, responses were smaller in black than non-black patients. There were no age- or gender-related differences in response.

The peak antihypertensive effect occurred 1 to 2 hours after a dose. The dose-related blood pressure response was accompanied by a dose-related increase in adverse effects [see ADVERSE REACTIONS (6)].

14.3 Hypertension With Type 2 Diabetes Mellitus

In a double-blind study (GEMINI), carvedilol, added to an ACE inhibitor or angiotensin receptor blocker, was evaluated in a population with mild-to-moderate hypertension and well controlled type 2 diabetes mellitus. The mean HbA1c at baseline was 7.2%. carvedilol was titrated to a mean dose of 17.5 mg twice daily and maintained for 5 months. Carvedilol had no adverse effect on glycemic control, based on HbA1c measurements (mean change from baseline of 0.02%, 95% CI -0.06 to 0.10, p = NS) [see WARNINGS AND PRECAUTIONS (5.6)].

16. HOW SUPPLIED/STORAGE AND HANDLING

Carvedilol Tablets USP, 6.25 mg are white to off-white, round, biconvex, beveled edge, film-coated tablets debossed with 'ZC40' on one side and plain on other side and are supplied as follows:

NDC-63187-424-30 in bottles of 30 tablets

NDC-63187-424-60 in bottles of 60 tablets

Storage:

Store at 20° to 25°C (68° to 77°F) [See USP Controlled Room Temperature].

Protect from moisture. Dispense in a tight, light-resistant container.

17. PATIENT COUNSELING INFORMATION

See FDA-Approved Patient Labeling []

17.1 Patient Advice

Patients taking carvedilol tablets should be advised of the following:

- Patients should take carvedilol tablets with food.
- Patients should not interrupt or discontinue using carvedilol tablets without a physician’s advice.
- Patients should consult their physician if they experience signs or symptoms of worsening heart failure such as weight gain or increasing shortness of breath.
- Patients may experience a drop in blood pressure when standing, resulting in dizziness and, rarely, fainting. Patients should sit or lie down when these symptoms of lowered blood pressure occur.
- If experiencing dizziness or fatigue, patients should avoid driving or hazardous tasks.
- Patients should consult a physician if they experience dizziness or faintness, in case the dosage should be adjusted.
- Diabetic patients should report any changes in blood sugar levels to their physician.
- Contact lens wearers may experience decreased lacrimation.

17.2 FDA-Approved Patient Labeling

Patient labeling is provided separately.

Manufactured by:
Cadila Healthcare Ltd.
India
Distributed by:
Zydus Pharmaceuticals USA Inc.
Pennington, NJ 08534
Rev.: 04/14
Revision Date: 2014/04/17

Repackaged by:
Proficient Rx LP
Thousand Oaks, CA 91320

PHARMACIST-DETACH HERE AND GIVE INSTRUCTIONS TO PATIENT

------------------------------------------------------------------------------------------------------------

PATIENT INFORMATION

CARVEDILOL TABLETS, USP

Read the Patient Information that comes with carvedilol tablets before you start taking it and each time you get a refill. There may be new information. This information does not take the place of talking with your doctor about your medical condition or your treatment. If you have any questions about carvedilol tablets, ask your doctor or pharmacist.

WHAT IS CARVEDILOL?

Carvedilol is a prescription medicine that belongs to a group of medicines called "beta-blockers". Carvedilol tablets are used, often with other medicines, for the following conditions:

- To treat patients with high blood pressure (hypertension)
- To treat patients who had a heart attack that worsened how well the heart pumps

Carvedilol tablets are not approved for use in children under 18 years of age.

WHO SHOULD NOT TAKE CARVEDILOL TABLETS?

Do not take carvedilol tablet if you:

- Have severe heart failure and are hospitalized in the intensive care unit or require certain intravenous medications that help support circulation (inotropic medications)
- Are prone to asthma or other breathing problems
- Have a slow heartbeat or a heart that skips a beat (irregular heartbeat)
- Have liver problems
- Are allergic to any of the ingredients in carvedilol tablets. The active ingredient is carvedilol. See the end of this leaflet for a list of all the ingredients in carvedilol tablets.

WHAT SHOULD I TELL MY DOCTOR BEFORE TAKING CARVEDILOL TABLETS?

Tell your doctor about all of your medical conditions, including if you:

- Have asthma or other lung problems (such as bronchitis or emphysema)
- Have problems with blood flow in your feet and legs (peripheral vascular disease) carvedilol tablets can make some of your symptoms worse.
- Have diabetes
- Have thyroid problems
- Have a condition called pheochromocytoma
- Have had severe allergic reactions
- Are pregnant or trying to become pregnant. It is not known if carvedilol tablets are safe for your unborn baby. You and your doctor should talk about the best way to control your high blood pressure during pregnancy.
- Are breastfeeding. It is not known if carvedilol passes into your breast milk. You should not breastfeed while using carvedilol tablets.
- Are scheduled for surgery and will be given anesthetic agents
- Are taking prescription or non-prescription medicines, vitamins, and herbal supplements. Carvedilol tablets and certain other medicines can affect each other and cause serious side effects. Carvedilol tablets may affect the way other medicines work. Also, other medicines may affect how well carvedilol tablets works

Keep a list of all the medicines you take. Show this list to your doctor and pharmacist before you start a new medicine.

HOW SHOULD I TAKE CARVEDILOL TABLETS?

It is important for you to take your medicine every day as directed by your doctor. If you stop taking carvedilol tablets suddenly, you could have chest pain and/or a heart attack. If your doctor decides that you should stop taking carvedilol tablets, your doctor may slowly lower your dose over a period of time before stopping it completely.

- Take carvedilol tablets exactly as prescribed. Your doctor will tell you how many tablets to take and how often. In order to minimize possible side effects, your doctor might begin with a low dose and then slowly increase the dose.
- Do not stop taking carvedilol tablets and do not change the amount of carvedilol tablets you take without talking to your doctor.
- Tell your doctor if you gain weight or have trouble breathing while taking carvedilol tablets.
- Take carvedilol tablets with food.
- If you miss a dose of carvedilol tablets, take your dose as soon as you remember, unless it is time to take your next dose. Take your next dose at the usual time. Do not take 2 doses at the same time.
- If you take too much carvedilol tablets, call your doctor or poison control center right away.

WHAT SHOULD I AVOID WHILE TAKING CARVEDILOL TABLETS?

Carvedilol tablets can cause you to feel dizzy, tired, or faint. Do not drive a car, use machinery, or do anything that needs you to be alert if you have these symptoms.

WHAT ARE POSSIBLE SIDE EFFECTS OF CARVEDILOL TABLETS?

- Low blood pressure (which may cause dizziness or fainting when you stand up). If these happen, sit or lie down right away and tell your doctor.
- Tiredness. If you feel tired or dizzy you should not drive, use machinery, or do anything that needs you to be alert.
- Slow heartbeat
- Changes in your blood sugar. If you have diabetes, tell your doctor if you have any changes in your blood sugar levels.
- Carvedilol tablets may hide some of the symptoms of low blood sugar, especially a fast heartbeat.
- Carvedilol tablets may mask the symptoms of hyperthyroidism (overactive thyroid).
- Worsening of severe allergic reactions.
- Rare but serious allergic reactions (including hives or swelling of the face, lips, tongue, and/or throat that may cause difficulty in breathing or swallowing) have happened in patients who were on carvedilol. These reactions can be life-threatening.

Other side effects of carvedilol tablets include shortness of breath, weight gain, diarrhea, and fewer tears or dry eyes that become bothersome if you wear contact lenses. Rare serious allergic reactions have happened in patients who were on carvedilol.

Call your doctor if you have any side effects that bother you or don't go away.

Call your doctor for medical advice about side effects. You may report side effects to FDA at 1-800-FDA-1088.

How should I store carvedilol tablets?

- Store carvedilol tablets at 20º to 25 º C (68 º to 77 ºF). Keep the tablets dry.
- Safely, throw away carvedilol tablets that are out of date or no longer needed.
- Keep carvedilol tablets and all medicines out of the reach of children.

GENERAL INFORMATION ABOUT CARVEDILOL TABLETS

Medicines are sometimes prescribed for conditions other than those described in patient information leaflets. Do not use carvedilol tablets for a condition for which it was not prescribed. Do not give carvedilol tablets to other people, even if they have the same symptoms you have. It may harm them.

This leaflet summarizes the most important information about carvedilol tablets. If you would like more information, talk with your doctor. You can ask your doctor or pharmacist for information about carvedilol tablets that is written for healthcare professionals. Please address medical inquiries to, (MedicalAffairs@zydususa.com) Tel.: 1-877-993-8779.

WHAT ARE THE INGREDIENTS IN CARVEDILOL TABLETS, USP?

Active Ingredient: Carvedilol, USP

Inactive Ingredients: Colloidal silicon dioxide, crospovidone, hypromellose, lactose monohydrate, magnesium stearate, polyethylene glycol, povidone, talc, and titanium dioxide.

Carvedilol tablets come in the following strengths: 3.125 mg, 6.25 mg, 12.5 mg and 25 mg

What is high blood pressure (hypertension)?

Blood pressure is the force of blood in your blood vessels when your heart beats and when your heart rests. You have high blood pressure when the force is too much. High blood pressure makes the heart work harder to pump blood through the body and causes damage to blood vessels. Carvedilol can help your blood vessels relax so your blood pressure is lower. Medicines that lower blood pressure may lower your chance of having a stroke or heart attack.